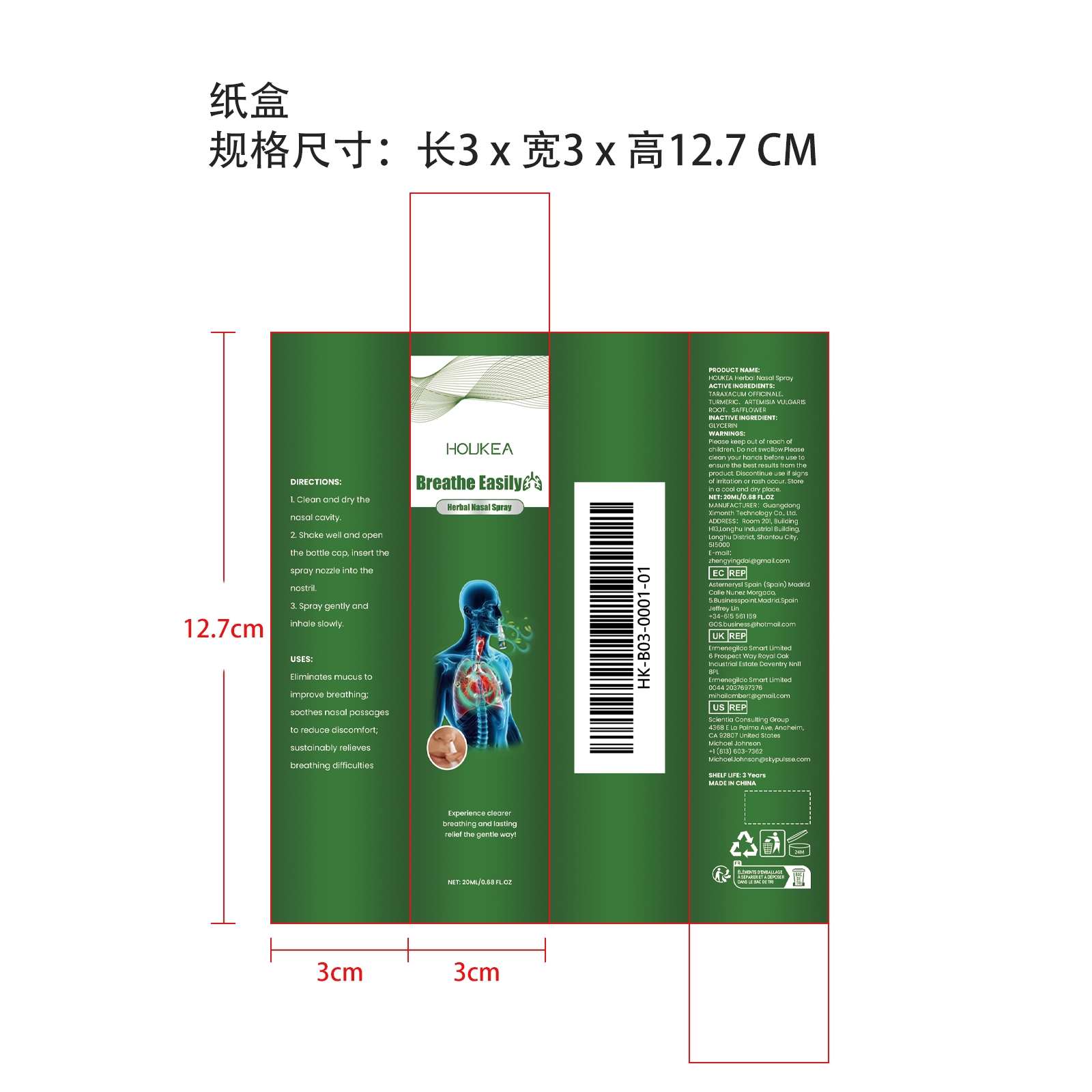 DRUG LABEL: HOUKEA Herbal Nasal
NDC: 84660-089 | Form: SPRAY
Manufacturer: Guangdong Ximonth Technology Co., Ltd.
Category: otc | Type: HUMAN OTC DRUG LABEL
Date: 20241029

ACTIVE INGREDIENTS: SAFFLOWER 3 mg/20 mg; ARTEMISIA VULGARIS ROOT 3 mg/20 mg; TARAXACUM OFFICINALE 6 mg/20 mg; TURMERIC 2 mg/20 mg
INACTIVE INGREDIENTS: GLYCERIN 6 mg/20 mg

ACTIVE INGREDIENTS

TARAXACUM OFFICINALE、 TURMERIC、 ARTEMISIA VULGARIS ROOT、 SAFFLOWER

PURPOSE

Eliminates mucus to improve breathing; soothes nasal passages to reduce discomfort; sustainably relieves breathing difficulties

USES

1. Clean and dry the nasal cavity.

2. Shake well and open the bottle cap, insert the spray nozzle into the nostril.

3. Spray gently and inhale slowly.

WARNINGS

Please keep out of reach of children. Do not swallow.Please clean your hands before use to ensure the best results from the product. Discontinue use if signs of irritation or rash occur. Store in a cool and dry place.

STOP USE

Discontinue use if signs of irritation or rash occur.

DO NOT USE

Discontinue use if signs of irritation or rash occur.

KEEP OUT OF REACH OF CHILDREN

Please keep out of reach of children. Do not swallow.

STORAGE AND HANDLING

Store in a cool and dry place.

INACTIVE INGREDIENT

GLYCERIN